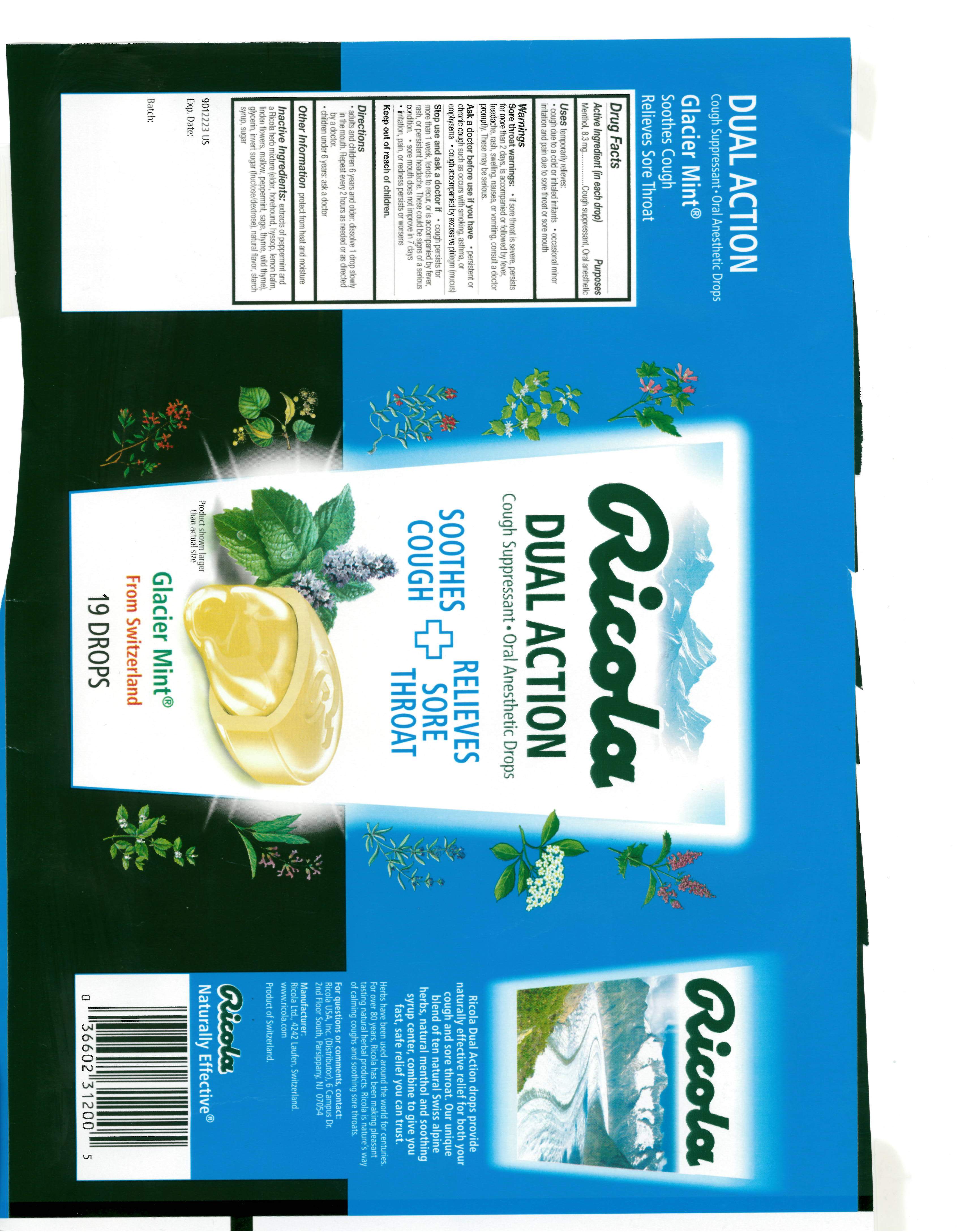 DRUG LABEL: DUAL ACTION GLACIER MINT COUGH SUPPRESSANT ORAL ANESTHETIC
NDC: 63667-603 | Form: LOZENGE
Manufacturer: Ricola USA Inc.
Category: otc | Type: HUMAN OTC DRUG LABEL
Date: 20241210

ACTIVE INGREDIENTS: MENTHOL 8.3 mg/1 1
INACTIVE INGREDIENTS: SUCROSE; GLYCERIN

DUAL ACTION GLACIER MINT SUPPRESSANT ORAL ANESTHETIC

Drug Facts

Purpose

Cough suppressant, Oral anesthetic

Active Ingredient (in each drop)

Menthol, 8.3 mg

Uses

temporarily relieves:

- cough due to a cold or inhaled irritants
- occasional minor irritation and pain due to sore throat or sore mouth

Warnings

Sore throat warnings:

- if sore throat is severe, persists for more than 2 days, is accompanied or followed by fever, headache, rash, swelling, nausea, or vomiting, consult a doctor promptly. These may be serious.

Ask doctor before use if you have

- persistent chronic cough such as occurs with smoking, asthma, or emphysema
- cough accompanied by excessive phlegm (mucus)

Stop use and ask a doctor if

- cough persists for more than 1 week, tends to recur, or is accompanied by fever, rash, or persistent headache. These could be signs of a serious condition.
- sore mouth does not improve in 7 days
- irritation, pain, or redness persists or worsens

Directions

- adults and children 6 years and older: dissolve 1 drop slowly in the mouth. Repeat every 2 hours as needed or as directed by a doctor
- children under 6 years: ask a doctor

Other Information

protect from heat and moisture

Inactive Ingredients

extracts of peppermint and a Ricola herb mixture (elder, horehound, hyssop, lemon balm, linden flowers, mallow, peppermint, sage, thyme, wild thyme), glycerin, invert sugar (fructose/dextrose), natural flavor, starch syrup, sugar